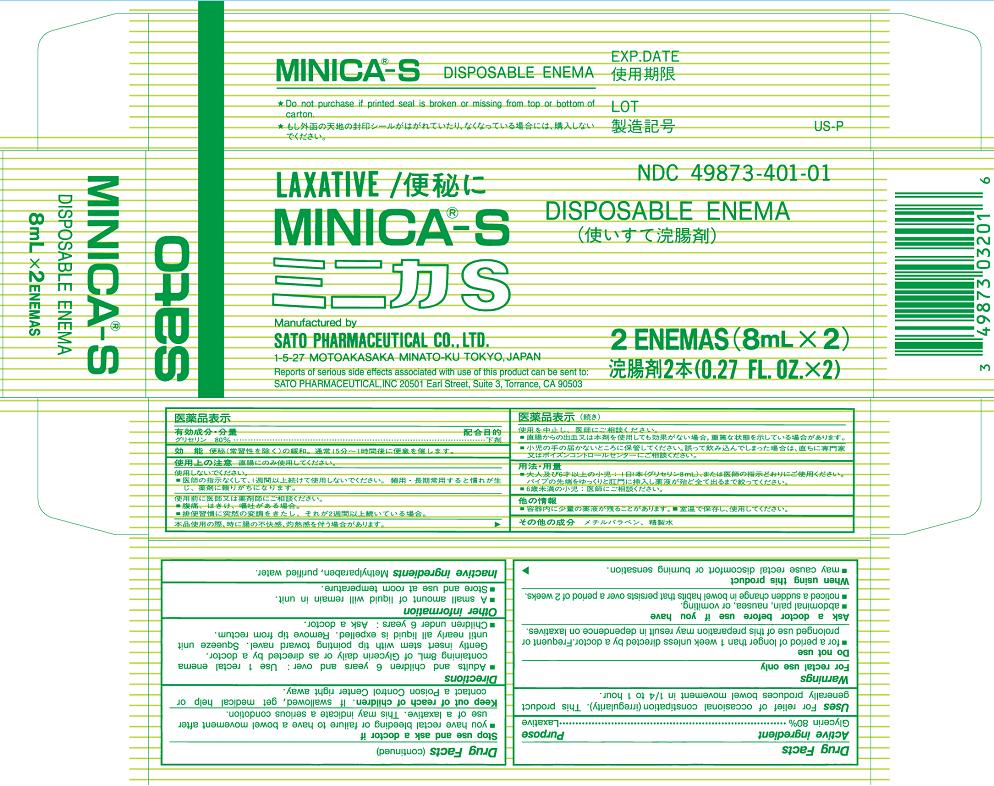 DRUG LABEL: MINICA-S
NDC: 49873-401 | Form: ENEMA
Manufacturer: Sato Pharmaceutical Co., Ltd.
Category: otc | Type: HUMAN OTC DRUG LABEL
Date: 20231207

ACTIVE INGREDIENTS: GLYCERIN 80 mL/100 mL
INACTIVE INGREDIENTS: METHYLPARABEN; WATER

Minica-S

Active ingredient Glycerin 80%

Purpose Laxative

INDICATIONS AND USAGE

Uses For relief of occasional consipation (irregularily). This product generally produces bowel movement in 1/4 to 1 hour.

Warnings
For rectal use only

Do not use
■for a period of longer than 1 week unless directed by a doctor. Frequent or prolonged use of this preparation may result in dependence on laxatives.

Ask a doctor before use if you have
■abdominal pain, nausea, or vomiting.
■noticed a sudden change in bowel habits that persists over a period of 2 weeks.

When using this product
■may cause rectal discomfort or burning sensation.

Stop use and ask a doctor if
■you have rectal bleeding or failure to have a bowel movement after use of a laxative. This may indicate a serious condition.

Keep out of reach of children. If swallowed, get medical help or contact a Poison Control Center right away.

Directions
■Adults and children 6 years and over: Use 1 rectal enema containing 8 mL of Glycerin daily or as directed by a doctor.
Gently insert stem with tip pointing toward navel. Squeeze unit until nearly all liquid is expelled. Remove tip from rectum.
■Children under 6 years: Ask a doctor.

Other information
■A small amount of liquid will remain in unit.
■Store and use at room temperature.

Inactive ingredients Methylparaben, purified water.